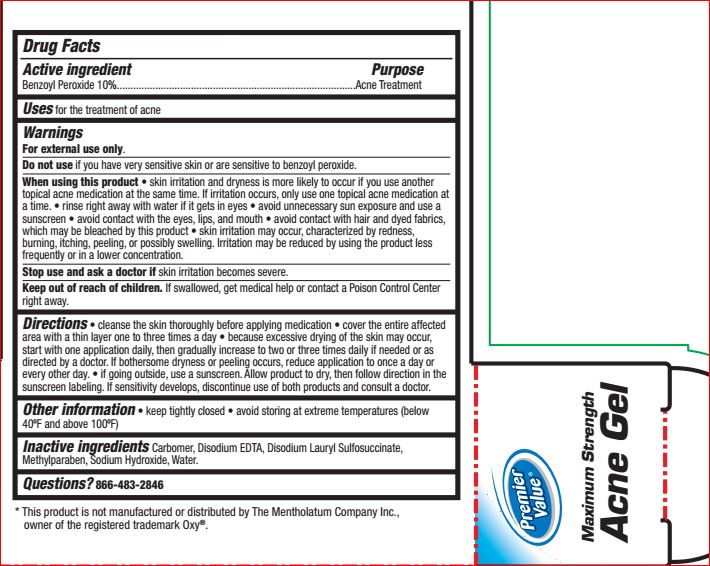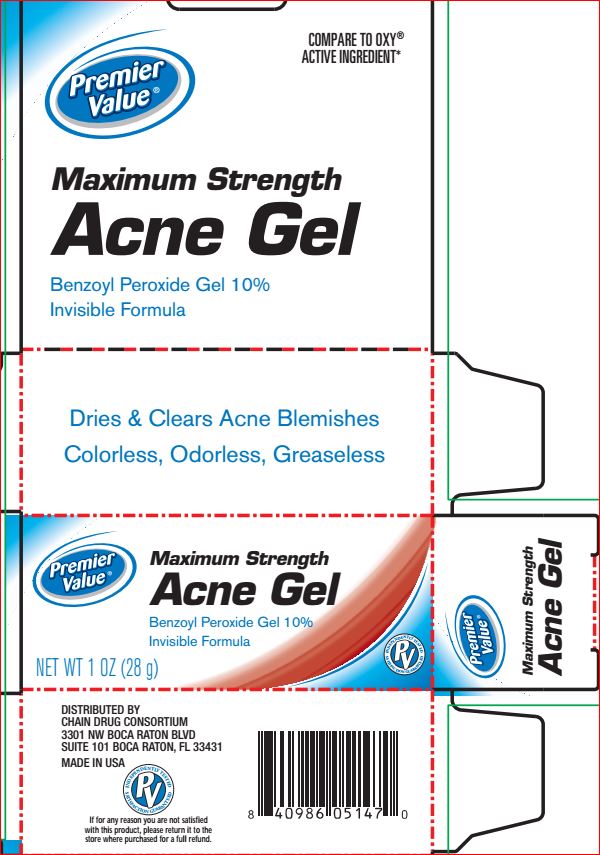 DRUG LABEL: Maximum Strength Acne
NDC: 68016-272 | Form: GEL
Manufacturer: Premier Value
Category: otc | Type: HUMAN OTC DRUG LABEL
Date: 20180814

ACTIVE INGREDIENTS: Benzoyl Peroxide 10 g/100 g
INACTIVE INGREDIENTS: Water; Disodium Lauryl Sulfosuccinate; CARBOMER HOMOPOLYMER TYPE C (ALLYL PENTAERYTHRITOL CROSSLINKED); Methylparaben; EDETATE DISODIUM; Sodium Hydroxide

Drug Facts

Active ingredient Purpose
Benzoyl Peroxide 10%.............................Acne Treatment

INDICATIONS AND USAGE

Uses for the treatment of acne

Warnings
For external use only.
Do not use if you have very sensitive skin or are sensitive to benzoyl peroxide.
When using this product • skin irritation and dryness is more likely to occur if you use another
topical acne medication at the same time. If irritation occurs, only use one topical acne medication
at a time. • rinse right away with water if it gets in eyes • avoid unnecessary sun exposure and use
a sunscreen • avoid contact with the eyes, lips, and mouth • avoid contact with hair and dyed
fabrics, which may be bleached by this product • skin irritation may occur, characterized by
redness, burning, itching, peeling, or possibly swelling. Irritation may be reduced by using the
product less frequently or in a lower concentration.
Stop use and ask a doctor if skin irritation becomes severe.
Keep out of reach of children. If swallowed, get medical help or contact a Poison Control Center
right away

DOSAGE AND ADMINISTRATION

Directions • cleanse the skin thoroughly before applying medication • cover the entire
affected area with a thin layer one to three times a day • because excessive drying of the skin
may occur, start with one application daily, then gradually increase to two or three times daily
if needed or as directed by a doctor. If bothersome dryness or peeling occurs, reduce
application to once a day or every other day. • if going outside, use a sunscreen. Allow product
to dry, then follow direction in the sunscreen labeling. If sensitivity develops, discontinue use of
both products and consult a doctor.

INACTIVE INGREDIENT

Inactive ingredients Carbomer, Disodium EDTA, Disodium Lauryl Sulfosuccinate,
Methylparaben, Sodium Hydroxide, Water.